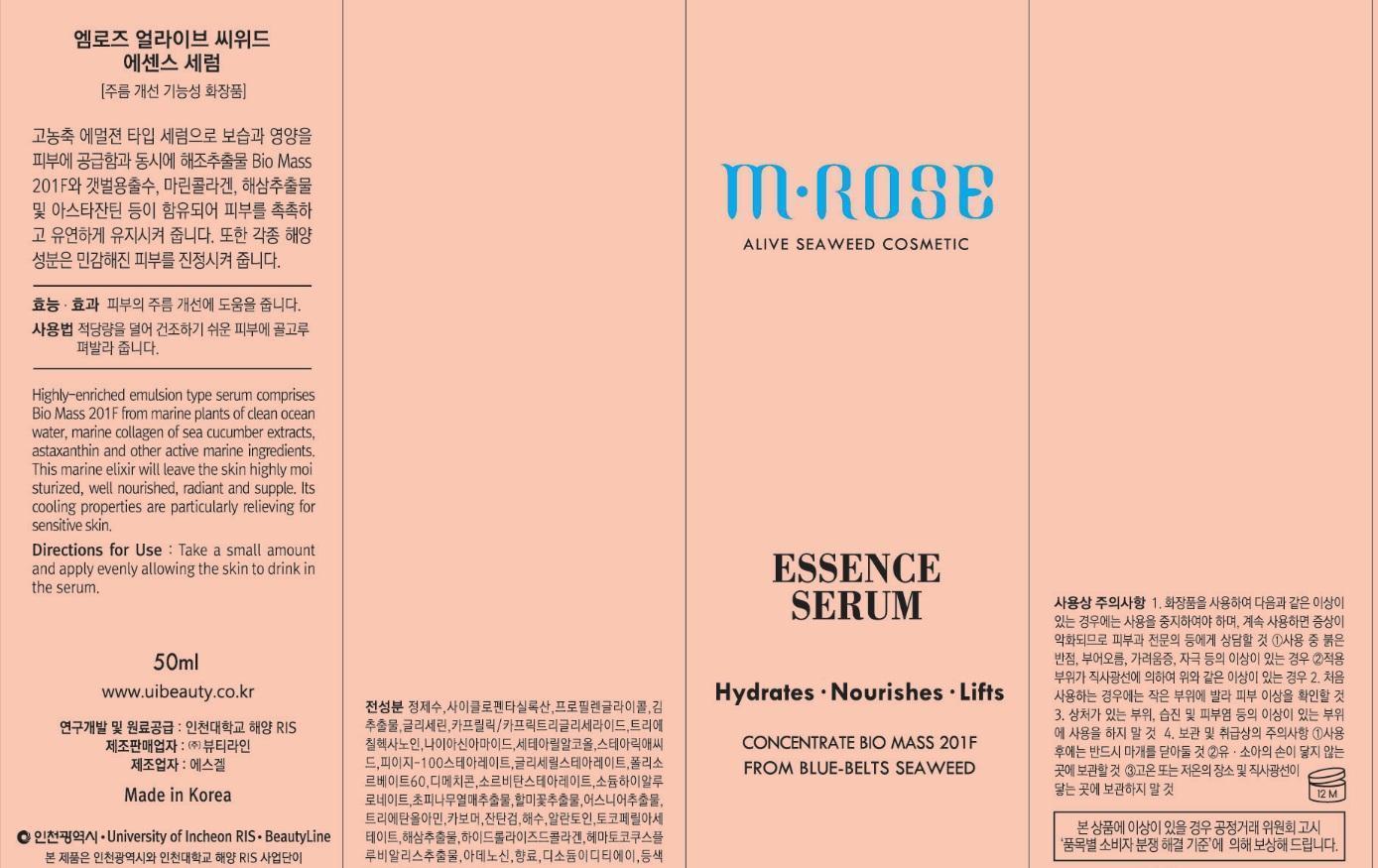 DRUG LABEL: M-Rose Seaweed Essence Serum
NDC: 69327-8001 | Form: CREAM
Manufacturer: Beauty Line Co., Ltd.
Category: otc | Type: HUMAN OTC DRUG LABEL
Date: 20141025

ACTIVE INGREDIENTS: ALLANTOIN 1 g/100 mL
INACTIVE INGREDIENTS: WATER; NIACINAMIDE; HYALURONATE SODIUM

Drug Facts

ACTIVE INGREDIENT

allantoin

INACTIVE INGREDIENT

water, propylene glycol, cetearyl alcohol, niacinamide, sodium hyaluronate, sorbitan stearate, dimethicon, etc

PURPOSE

anti-wrinkle
skin protectant

keep out or reach of the children

INDICATIONS AND USAGE

apply a moderate amount evenly after soothng mist has been fully absorbed

WARNINGS

-If in contact with the eyes, wash out thoroughty with water If the symptoms are servere, seek medical advice immediately
-This product is for exeternal use only. Do not use for internal use
-If possible, avoid direct sunlight and store in cool and area of low humidity
-In order to maintain the quality of the product and avoid misuse
-Avoid placing the product near fire and store out in reach of children

DOSAGE AND ADMINISTRATION

for external use only